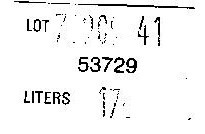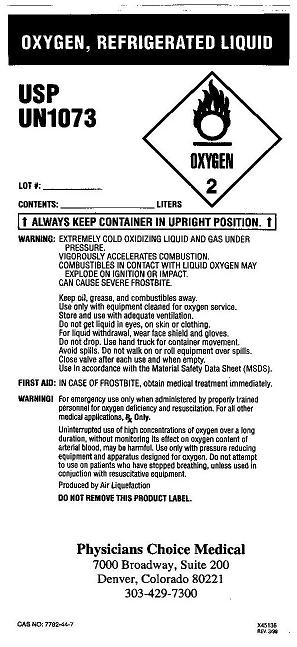 DRUG LABEL: Oxygen
NDC: 62956-0001 | Form: GAS
Manufacturer: Physician's Choice Medical, LLC
Category: prescription | Type: HUMAN PRESCRIPTION DRUG LABEL
Date: 20091029

ACTIVE INGREDIENTS: Oxygen 99 L/100 L

Oxygen